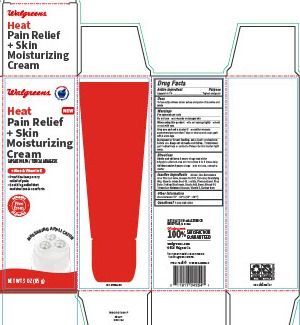 DRUG LABEL: Heat Pain Relief
NDC: 0363-6263 | Form: CREAM
Manufacturer: Walgreen Company
Category: otc | Type: HUMAN OTC DRUG LABEL
Date: 20250328

ACTIVE INGREDIENTS: CAPSAICIN 0.1 g/100 g
INACTIVE INGREDIENTS: CARBOMER 940; POLYSORBATE 60; ALMOND OIL; LECITHIN, SUNFLOWER; CETOSTEARYL ALCOHOL; SODIUM BICARBONATE; PHENOXYETHANOL; STEARIC ACID; AVOCADO OIL; GLYCERIN; TETRASODIUM GLUTAMATE DIACETATE; ALPHA-TOCOPHEROL; XANTHAN GUM; ALCOHOL; JOJOBA OIL; ALOE VERA LEAF; SHEA BUTTER

6263 - Walgreen

Drug Facts

Active ingredient

Capsaicin 0.1%

Purpose

Topical analgesic

Uses

Temporarily relieves minor aches and pains of muscles and joints

WARNINGS

For external use only

DO NOT USE

- on wounds or damaged skin

WHEN USING

- Do not bandage tightly
- Avoid contact with eyes

STOP USE

- condition worsens
- symptoms last more than 7 days or clear up and occur again within a few days

PREGNANCY OR BREAST FEEDING

If pregnant or breast feeding, ask a health professional before use.

Keep out of reach of children.

OVERDOSAGE

If swallowed, get medical help or contact a Posion Control Center right away.

Directions

Adults and children 2 years of age and older

- Apply to affected area not more than 3 to 4 times daily

Children under 2 years of age

- do not use, consult a doctor

INACTIVE INGREDIENT

Alcohol, Aloe Barbadensis Inner Fillet Leaf Juice, Avocado Fruit Oil, Carbomer, Emulsifying Wax, Glycerin, Jojoba Seed Oil, Lecithin, Phenoxyethanol, Shea Butter, Sodium Bicarbonate, Stearic Acid, Sweet Almond Oil, Tetrasodium Glutamate Diacetate, Vitamin E, Xanthan Gum

Other information

store between 15° -30°C (59° - 86°F)

QUESTIONS

1-800-925-4733

DISTRIBUTED BY: WALGREEN CO. DEERFIELD, IL 60015

Walgreens 100% SATISFACTION GUARNATEED

walgreens.com

©2024 Walgreen Co.

NDC 0363-6263-07

PACKAGE LABEL

Walgreens

Heat Pain Relief + Skin Moisturizing Cream

CAPSAICIN 0.1% / TOPICAL ANALGESIC

+ Aloe & Vitamin E

Provides temporary relief of pain

Soothing relief that moisturizes & comforts

Free from Parabens, Fragrance

NET WT 3 OZ (85 g)